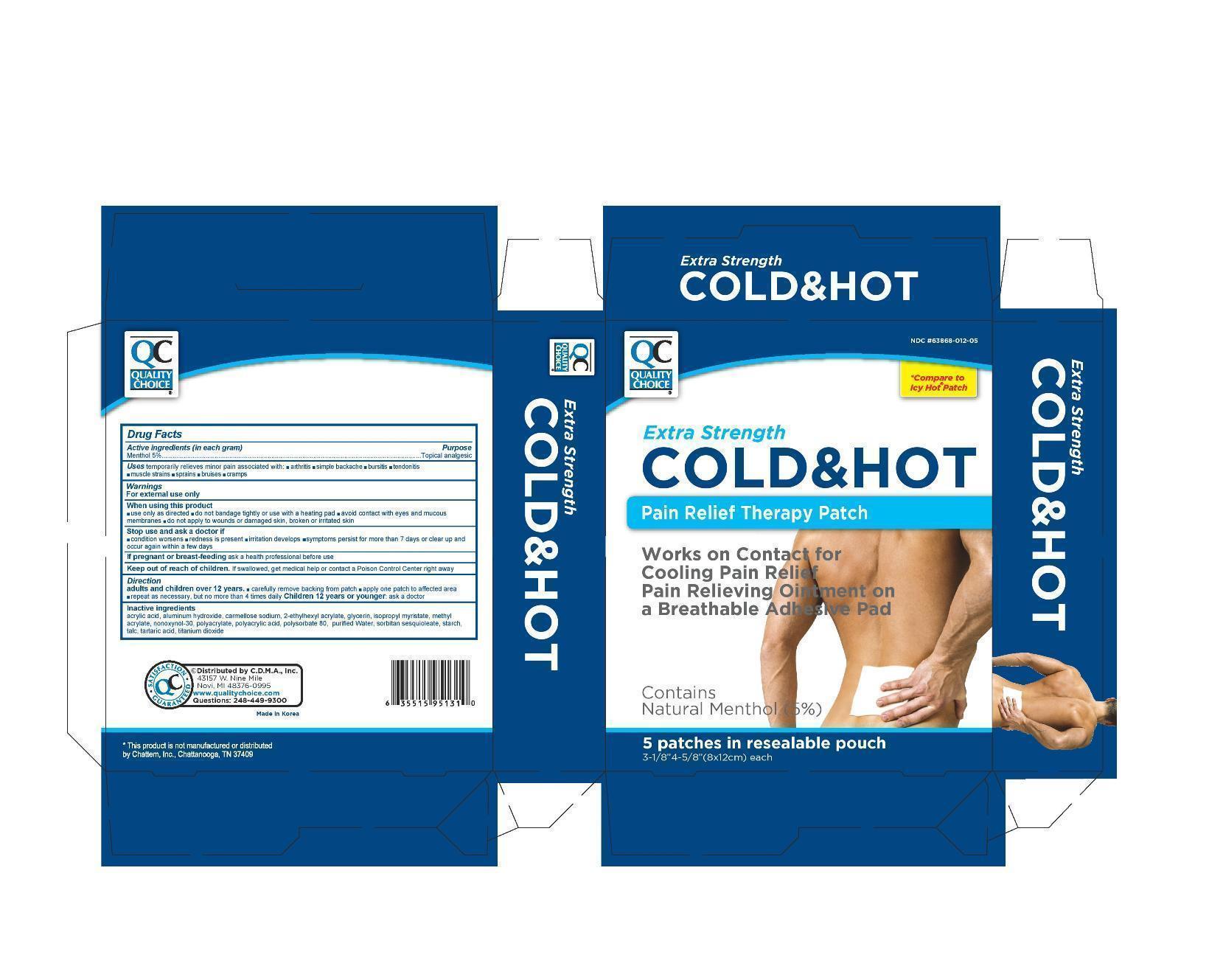 DRUG LABEL: QC Cold and Hot Pain Relief
NDC: 63868-012 | Form: PATCH
Manufacturer: CHAIN DRUG MARKETING ASSOCIATION INC
Category: otc | Type: HUMAN OTC DRUG LABEL
Date: 20121107

ACTIVE INGREDIENTS: MENTHOL 400 mg/1 1
INACTIVE INGREDIENTS: ACRYLIC ACID; ALUMINUM HYDROXIDE; CARBOXYMETHYLCELLULOSE SODIUM; GLYCERIN; ISOPROPYL MYRISTATE; METHYL ACRYLATE; NONOXYNOL-30; POLYSORBATE 80; SORBITAN SESQUIOLEATE; TALC; TARTARIC ACID; TITANIUM DIOXIDE; WATER

Drug Facts

Active Ingredient

Menthol 5.0%

Purpose

Topical Analgesic

Uses

temporarily relieves minor pain associated with

- arthritis
- simple backache
- bursitis
- tendonitis
- muscle strains
- sprains
- bruises
- cramps

Warnings

For external use only

When using this product

- use only as directed
- avoid contact with eyes and mucous membranes
- do not bandage tightly or use with a heating pad
- do not apply to wounds or damaged skin, broken or irritated skin

Stop use and ask a doctor if

- condition worsens
- redness is present
- irritation develops
- symptoms persist for more than 7 days or clear up and occur again within a few days

If pregnant or breast-feeding,

ask a health professional before use

Keep out of reach of children.

If swallowed, get medical help or contact a Poison Control Center right away.

Directions

Adults and children over 12 years:

- carefully remove backing from patch
- apply one patch to affected area
- repeat as necessary, but no more than 4 times daily

Children 12 years or younger: ask a doctor

Inactive ingredients

Acrylic Acid, Aluminum Hydroxide, Carmellose sodium, 2-Ethylhexyl Acrylate, Glycerin, Isopropyl Myristate, Methyl Acrylate, Nonoxymol-30, Sodium Polyacrylate, Polyacrylic Acid, Polysorbate 80, Purified Water, Sorbitan Sesquioleate, Starch, Talc, Tartaric acid, Titanium Dioxide

package label

QC Cold and Hot Patch